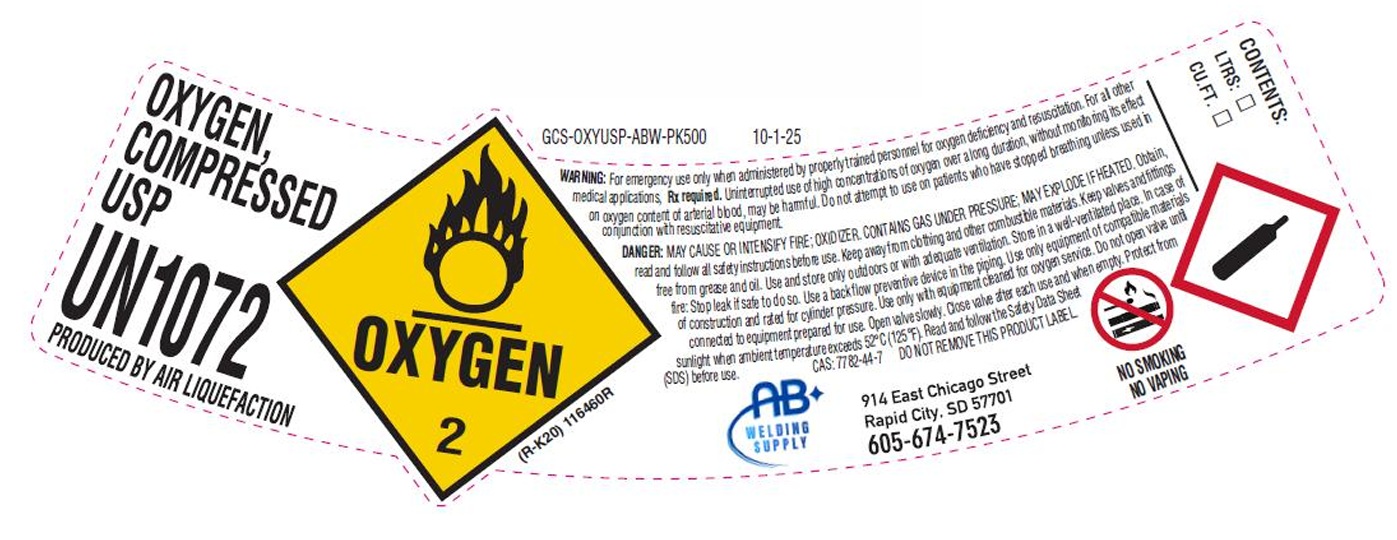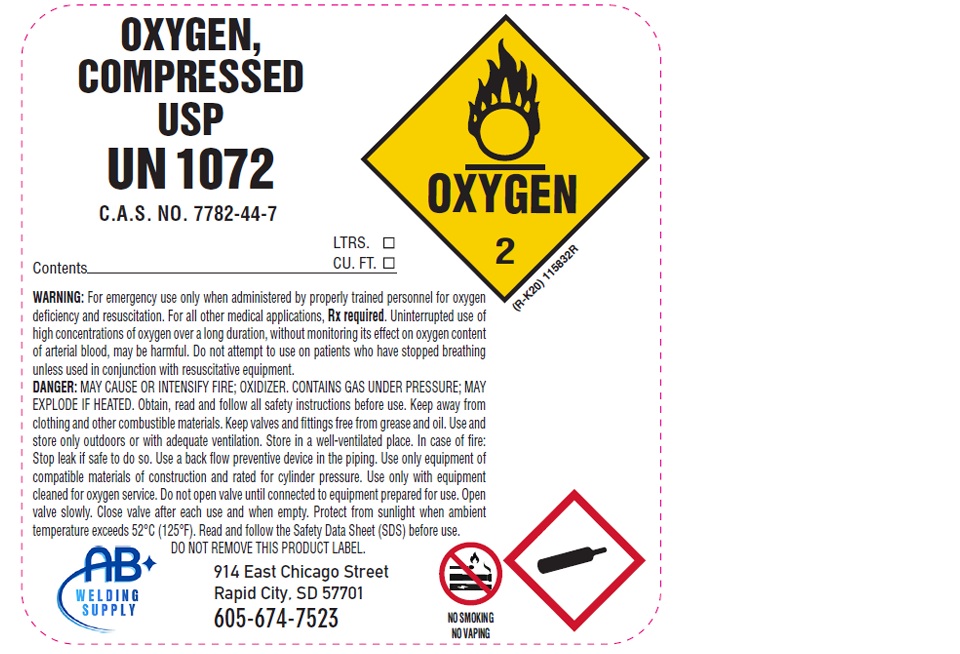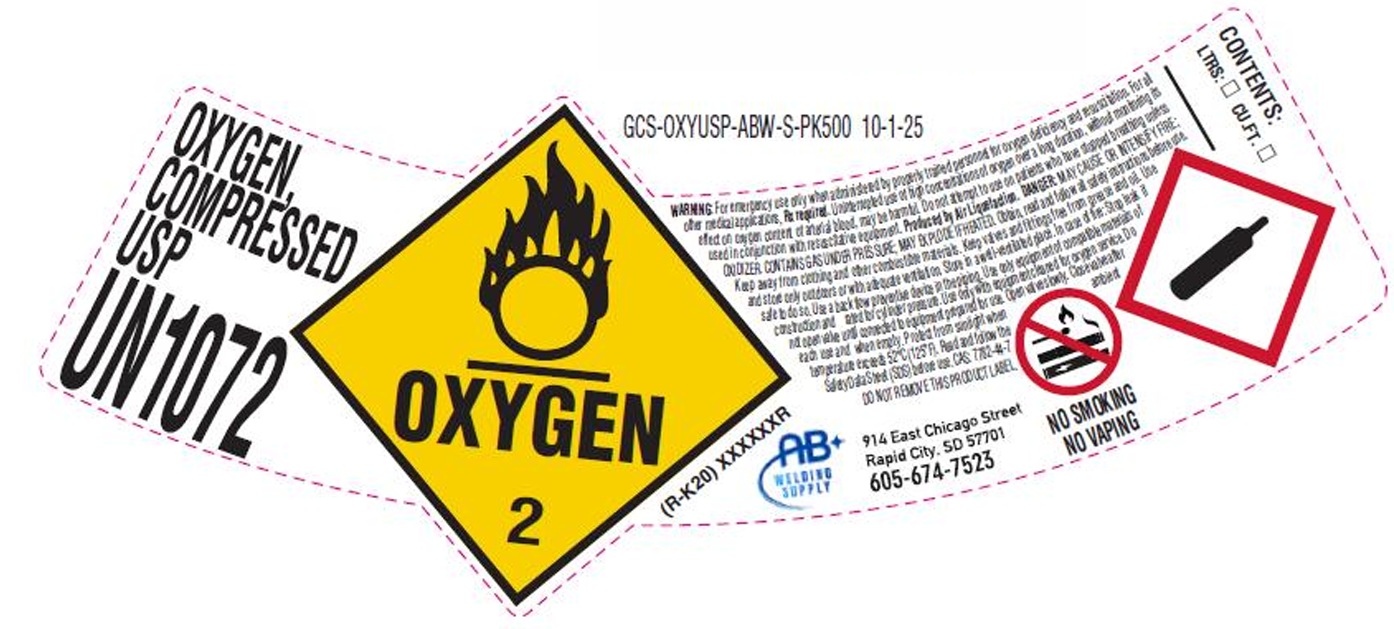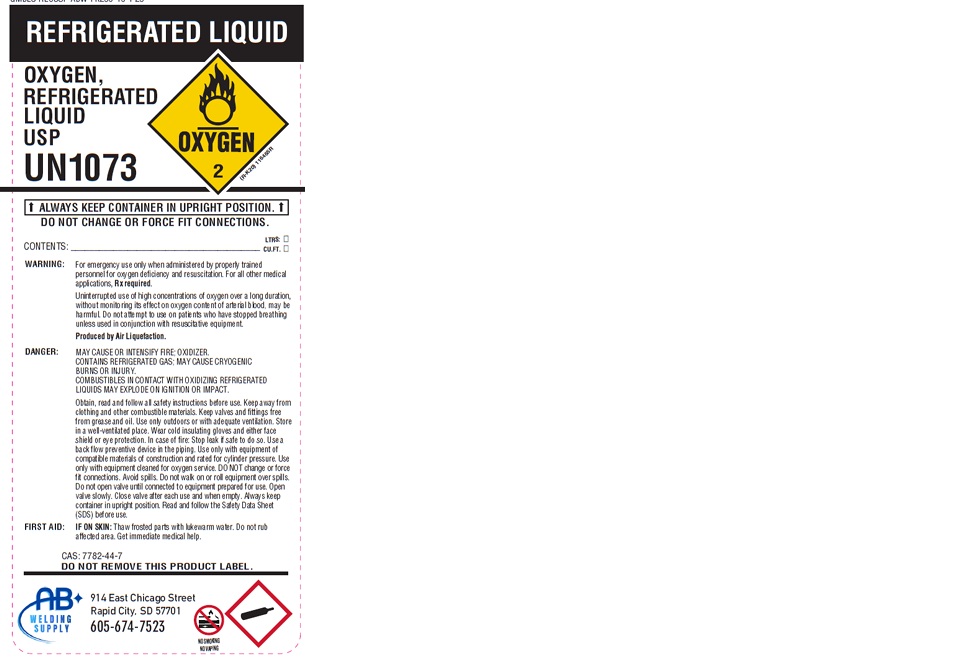 DRUG LABEL: Oxygen
NDC: 55728-011 | Form: GAS
Manufacturer: A & B Welding Supply Co.
Category: animal | Type: PRESCRIPTION ANIMAL DRUG LABEL
Date: 20251118

ACTIVE INGREDIENTS: Oxygen 990 mL/1 L

Oxygen Labels

PACKAGE LABEL

OXYGEN, COMPRESSED USP
UN1072
PRODUCED BY AIR LIQUEFACTION
WARNING: For emergency use only when administered by properly trained personnel for oxygen deficiency and resuscitation. For all other medical applications, Rx required. Uninterrupted use of high concentrations of oxygen over a long duration, without monitoring its effect on oxygen content of arterial blood, may be harmful. Do not attempt to use on patients who have stopped breathing unless used in conjunction with resuscitative equipment.
DANGER: MAY CAUSE OR INTENSIFY FIRE; OXIDIZER. CONTAINS GAS UNDER PRESSURE; MAY EXPLODE IF HEATED. Obtain, read and follow all safety instructions before use. Keep away from clothing and other combustible materials. Keep valves and fittings free from grease and oil. Use and store only outdoors or with adequate ventilation. Store in a well-ventilated place. In case of fire: Stop leak if safe to do so. Use a back flow preventive device in the piping. Use only equipment of compatible materials of construction and rated for cylinder pressure. Use only with equipment cleaned for oxygen service. Do not open valve until connected to equipment prepared for use. Open valve slowly. Close valve after each use and when empty. Protect from sunlight when ambient temperature exceeds 52 C (125 F). Read and follow the Safety Data Sheet (SDS) before use. CAS: 7782-44-7 DO NOT REMOVE THIS PRODUCT LABEL.
AB WELDING SUPPLY
914 East Chicago Street
Rapid City, SD 57701
605-674-7523
NO SMOKING
NO VAPING
CONTENTS: LTRS: CU.FT.

PACKAGE LABEL

OXYGEN, COMPRESSED USP
UN1072
WARNING: For emergency use only when administered by properly trained personnel for oxygen deficiency and resuscitation. For all other medical applications, Rx required. Uninterrupted use of high concentrations of oxygen over a long duration, without monitoring its effect on oxygen content of arterial blood, may be harmful. Do not attempt to use on patients who have stopped breathing unless used in conjunction with resuscitative equipment. Produced by Air Liquefaction. DANGER: MAY CAUSE OR INTENSIFY FIRE; OXIDIZER. CONTAINS GAS UNDER PRESSURE; MAY EXPLOD IF HEATED. Obtain, read and follow all safety instructions before use. Keep away from clothing and other combustible materials. Keep valves and fittings free from grease and oil. Use and store only outdoors or with adequate ventilation. Store in a well-ventilated place. In case of fire: Stop leak if safe to do so. Use a back flow preventive device in the piping. Use only equipment of compatible materials of construction and rated for cylinder pressure. Use only with equipment cleaned for oxygen service. Do not open valve until connected to equipment prepared for use. Open valve slowly. Close valve after each use and when empty. Protect from sunlight when ambient temperature exceeds 52 C (125 F). Read and follow the Safety Data Sheet (SDS) before use. CAS: 7782-44-7
DO NOT REMOVE THIS PRODUCT LABEL.
AB WELDING SUPPLY
914 East Chicago Street
Rapid City, SD 57701
605-674-7523
NO SMOKING
NO VAPING
CONTENTS: LTRS: CU.FT.

PACKAGE LABEL

OXYGEN, COMPRESSED USP
UN1072
C.A.S. NO. 7782-44-7
Contents LTRS. CU.FT.
WARNING: For emergency use only when administered by properly trained personnel for oxygen deficiency and resuscitation. For all other medical applications, Rx required. Uninterrupted use of high concentrations of oxygen over a long duration, without monitoring its effect on oxygen content of arterial blood, may be harmful. Do not attempt to use on patients who have stopped breathing unless used in conjunction with resuscitative equipment.
DANGER: MAY CAUSE OR INTENSIFY FIRE; OXIDIZER. CONTAINS GAS UNDER PRESSURE; MAY EXPLODE IF HEATED. Obtain, read and follow all safety instructions before use. Keep away from clothing and other combustible materials. Keep valves and fittings free from grease and oil. Use and store only outdoors or with adequate ventilation. Store in a well-ventilated place. In case of fire: Stop leak if safe to do so. Use a back flow preventive device in the piping. Use only with equipment of compatible materials of construction and rated for cylinder pressure. Use only with equipment cleaned for oxygen service. Do not open valve until connected to equipment prepared for use. Open valve slowly. Close valve after each use and when empty. Protect from sunlight when ambient temperature exceeds 52 C (125 F). Read and follow the Safety Data Sheet (SDS) before use.
DO NOT REMOVE THIS PRODUCT LABEL.
AB WELDING SUPPLY
914 East Chicago Street
Rapid City, SD 57701
605-674-7523
NO SMOKING
NO VAPING

PACKAGE LABEL

REFRIGERATED LIQUID
OXYGEN, REFRIGERATED LIQUID USP
UN1073
ALWAYS KEEP CONTAINER IN UPRIGHT POSITION.
DO NOT CHANGE OR FORCE FIT CONNECTIONS.
CONTENTS: LTRS: CU.FT.
WARNING: For emergency use only when administered by properly trained personnel for oxygen deficiency and resuscitation. For all other medical applications, Rx required.
Uninterrupted use of high concentrations of oxygen over a long duration, without monitoring its effect on oxygen content of arterial blood, may be harmful. Do not attempt to use on patients who have stopped breathing unless used in conjunction with resuscitative equipment.
Produced by Air Liquefaction.
DANGER: MAY CAUSE OR INTENSIFY FIRE; OXIDIZER. CONTAINS REFRIGERATED GAS; MAY CAUSE CRYOGENIC BURNS OR INJURY. COMBUSTIBLES IN CONTACT WITH OXIDIZING REFRIGERATED LIQUIDS MAY EXPLODE ON IGNITION OR IMPACT.
Obtain, read and follow all safety instructions before use. Keep away from clothing and other combustible materials. Keep valves and fittings free from grease and oil. Use only outdoors or with adequate ventilation. Store in a well-ventilated place. Wear cold insulating gloves and either face shield or eye protection. In case of fire: Stop leak if safe to do so. Use a back flow preventive device in the piping. Use only with equipment of compatible materials of construction and rated for cylinder pressure. Use only with equipment cleaned for oxygen service. DO NOT change or force fit connections. Avoid spills. Do not walk on or roll equipment over spills. Do not open valve until connected to equipment prepared for use. Open valve slowly. Close valve after each use and when empty. Always keep container in upright position. Read and follow the Safety Data Sheet (SDS) before use.
FIRST AID: IF ON SKIN: Thaw frosted parts with lukewarm water. Do not rub affected area. Get immediate medical help.
CAS: 7782-44-7
DO NOT REMOVE THIS PRODUCT LABEL.
AB WELDING SUPPLY
914 East Chicago Street
Rapid City, SD 57701
605-674-7523
NO SMOKING
NO VAPING